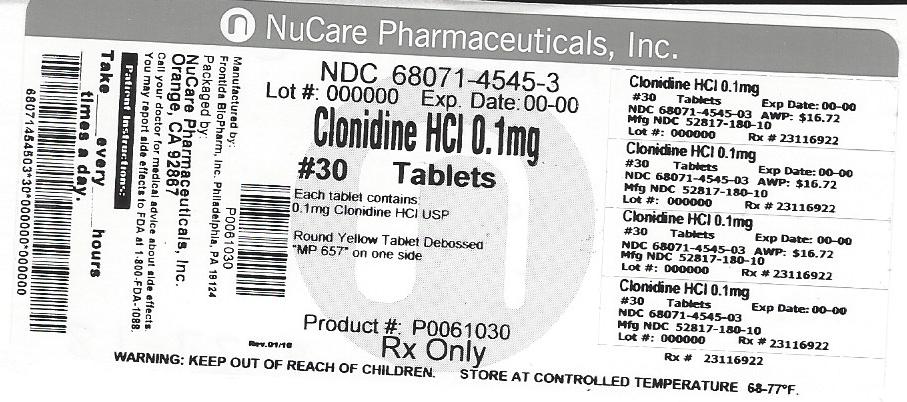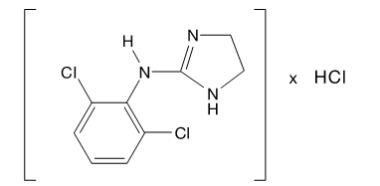 DRUG LABEL: Clonidine hydrochloride
NDC: 68071-4545 | Form: TABLET
Manufacturer: NuCare Pharmaceuticals,Inc.
Category: prescription | Type: HUMAN PRESCRIPTION DRUG LABEL
Date: 20260227

ACTIVE INGREDIENTS: CLONIDINE HYDROCHLORIDE 0.1 mg/1 1
INACTIVE INGREDIENTS: LACTOSE, UNSPECIFIED FORM; MAGNESIUM STEARATE; MICROCRYSTALLINE CELLULOSE; STARCH, PREGELATINIZED CORN; SODIUM STARCH GLYCOLATE TYPE A POTATO; D&C YELLOW NO. 10

Clonidine hydrochloride

Rx only

CLONIDINE HYDROCHLORIDE TABLETS USP

DESCRIPTION

Clonidine hydrochloride is a centrally acting alpha-agonist hypotensive agent available as tablets for oral administration in three dosage strengths: 0.1 mg, 0.2 mg and 0.3 mg. The 0.1 mg tablet is equivalent to 0.087 mg of the free base.

Clonidine hydrochloride tablets USP contain the following inactive ingredients: lactose, magnesium stearate, microcrystalline cellulose, pregelatinized starch, and sodium starch glycolate. The 0.1 mg also contains D&C yellow #10 aluminum lake, and the 0.3 mg contains D&C yellow #10 aluminum lake and FD&C blue #1 aluminum lake.

Clonidine hydrochloride is an imidazoline derivative and exists as a mesomeric compound. The chemical name is 2-(2,6-dichlorophenylamino)-2-imidazoline hydrochloride. The following is the structural formula:

C9H9Cl2N3 • HCl Mol. Wt. 266.56

Clonidine hydrochloride is an odorless, bitter, white, crystalline substance soluble in water and alcohol.

CLINICAL PHARMACOLOGY

Clonidine stimulates alpha-adrenoreceptors in the brain stem. This action results in reduced sympathetic outflow from the central nervous system and in decreases in peripheral resistance, renal vascular resistance, heart rate, and blood pressure. Clonidine hydrochloride tablets USP act relatively rapidly. The patient’s blood pressure declines within 30 to 60 minutes after an oral dose, the maximum decrease occurring within 2 to 4 hours. Renal blood flow and glomerular filtration rate remain essentially unchanged. Normal postural reflexes are intact; therefore, orthostatic symptoms are mild and infrequent.

Acute studies with clonidine hydrochloride in humans have demonstrated a moderate reduction (15% to 20%) of cardiac output in the supine position with no change in the peripheral resistance: at a 45° tilt there is a smaller reduction in cardiac output and a decrease of peripheral resistance. During long-term therapy, cardiac output tends to return to control values, while peripheral resistance remains decreased. Slowing of the pulse rate has been observed in most patients given clonidine, but the drug does not alter normal hemodynamic response to exercise.

Tolerance to the antihypertensive effect may develop in some patients, necessitating a reevaluation of therapy.

Other studies in patients have provided evidence of a reduction in plasma renin activity and in the excretion of aldosterone and catecholamines. The exact relationship of these pharmacologic actions to the antihypertensive effect of clonidine has not been fully elucidated.

Clonidine acutely stimulates growth hormone release in both children and adults, but does not produce a chronic elevation of growth hormone with long-term use.

Pharmacokinetics

The pharmacokinetics of clonidine is dose-proportional in the range of 100 to 600 mcg. The absolute bioavailability of clonidine on oral administration is 70% to 80%. Peak plasma clonidine levels are attained in approximately 1 to 3 hours.

Following intravenous administration, clonidine displays biphasic disposition with a distribution half-life of about 20 minutes and an elimination half-life ranging from 12 to 16 hours. The half-life increases up to 41 hours in patients with severe impairment of renal function. Clonidine crosses the placental barrier. It has been shown to cross the blood-brain barrier in rats.

Following oral administration about 40% to 60% of the absorbed dose is recovered in the urine as unchanged drug in 24 hours. About 50% of the absorbed dose is metabolized in the liver. Neither food nor the race of the patient influences the pharmacokinetics of clonidine.

The antihypertensive effect is reached at plasma concentrations between about 0.2 and 2.0 ng/mL in patients with normal excretory function. A further rise in the plasma levels will not enhance the antihypertensive effect.

INDICATIONS AND USAGE

Clonidine hydrochloride tablets USP are indicated in the treatment of hypertension. Clonidine hydrochloride tablets USP may be employed alone or concomitantly with other antihypertensive agents.

CONTRAINDICATIONS

Clonidine hydrochloride tablets USP should not be used in patients with known hypersensitivity to clonidine (see PRECAUTIONS).

WARNINGS

Withdrawal

Patients should be instructed not to discontinue therapy without consulting their physician. Sudden cessation of clonidine treatment has, in some cases, resulted in symptoms such as nervousness, agitation, headache, and tremor accompanied or followed by a rapid rise in blood pressure and elevated catecholamine concentrations in the plasma. The likelihood of such reactions to discontinuation of clonidine therapy appears to be greater after administration of higher doses or continuation of concomitant beta-blocker treatment and special caution is therefore advised in these situations. Rare instances of hypertensive encephalopathy, cerebrovascular accidents and death have been reported after clonidine withdrawal. When discontinuing therapy with clonidine hydrochloride tablets USP, the physician should reduce the dose gradually over 2 to 4 days to avoid withdrawal symptomatology.

An excessive rise in blood pressure following discontinuation of clonidine hydrochloride tablets USP therapy can be reversed by administration of oral clonidine hydrochloride or by intravenous phentolamine. If therapy is to be discontinued in patients receiving a beta-blocker and clonidine concurrently, the beta-blocker should be withdrawn several days before the gradual discontinuation of clonidine hydrochloride tablets USP.

Because children commonly have gastrointestinal illnesses that lead to vomiting, they may be particularly susceptible to hypertensive episodes resulting from abrupt inability to take medication.

PRECAUTIONS

General

In patients who have developed localized contact sensitization to clonidine-TTS, continuation of clonidine-TTS or substitution of oral clonidine hydrochloride therapy may be associated with the development of a generalized skin rash.

In patients who develop an allergic reaction to clonidine-TTS, substitution of oral clonidine hydrochloride may also elicit an allergic reaction (including generalized rash, urticaria, or angioedema).

The sympatholytic action of clonidine may worsen sinus node dysfunction and atrioventricular (AV) block, especially in patients taking other sympatholytic drugs. There are post-marketing reports of patients with conduction abnormalities and/or taking other sympatholytic drugs who developed severe bradycardia requiring IV atropine, IV isoproterenol and temporary cardiac pacing while taking clonidine.

In hypertension caused by pheochromocytoma, no therapeutic effect of clonidine hydrochloride tablets USP can be expected.

Perioperative Use

Administration of clonidine hydrochloride tablets USP should be continued to within 4 hours of surgery and resumed as soon as possible thereafter. Blood pressure should be carefully monitored during surgery and additional measures to control blood pressure should be available if required.

Information for Patients

Patients should be cautioned against interruption of clonidine hydrochloride tablets USP therapy without their physician’s advice.

Since patients may experience a possible sedative effect, dizziness, or accommodation disorder with use of clonidine, caution patients about engaging in activities such as driving a vehicle or operating appliances or machinery. Also, inform patients that this sedative effect may be increased by concomitant use of alcohol, barbiturates, or other sedating drugs.

Patients who wear contact lenses should be cautioned that treatment with clonidine hydrochloride tablets USP may cause dryness of eyes.

Drug Interactions

Clonidine may potentiate the CNS-depressive effects of alcohol, barbiturates or other sedating drugs. If a patient receiving clonidine hydrochloride is also taking tricyclic antidepressants, the hypotensive effect of clonidine may be reduced, necessitating an increase in the clonidine dose. If a patient receiving clonidine is also taking neuroleptics, orthostatic regulation disturbances (e.g., orthostatic hypotension, dizziness, fatigue) may be induced or exacerbated.

Monitor heart rate in patients receiving clonidine concomitantly with agents known to affect sinus node function or AV nodal conduction, e.g., digitalis, calcium channel blockers and beta-blockers. Sinus bradycardia resulting in hospitalization and pacemaker insertion has been reported in association with the use of clonidine concomitantly with diltiazem or verapamil.

Amitriptyline in combination with clonidine enhances the manifestation of corneal lesions in rats (see Toxicology).

Based on observations in patients in a state of alcoholic delirium it has been suggested that high intravenous doses of clonidine may increase the arrhythmogenic potential (QT-prolongation, ventricular fibrillation) of high intravenous doses of haloperidol. Causal relationship and relevance for clonidine oral tablets have not been established.

Toxicology

In several studies with oral clonidine hydrochloride, a dose-dependent increase in the incidence and severity of spontaneous retinal degeneration was seen in albino rats treated for six months or longer. Tissue distribution studies in dogs and monkeys showed a concentration of clonidine in the choroid.

In view of the retinal degeneration seen in rats, eye examinations were performed during clinical trials in 908 patients before, and periodically after, the start of clonidine therapy. In 353 of these 908 patients, the eye examinations were carried out over periods of 24 months or longer. Except for some dryness of the eyes, no drug-related abnormal ophthalmological findings were recorded and, according to specialized tests such as electroretinography and macular dazzle, retinal function was unchanged.

In combination with amitriptyline, clonidine hydrochloride administration led to the development of corneal lesions in rats within 5 days.

Carcinogenesis, Mutagenesis, Impairment of Fertility

Chronic dietary administration of clonidine was not carcinogenic to rats (132 weeks) or mice (78 weeks) dosed, respectively, at up to 46 or 70 times the maximum recommended daily human dose as mg/kg (9 or 6 times the MRDHD on a mg/m^2 basis). There was no evidence of genotoxicity in the Ames test for mutagenicity or mouse micronucleus test for clastogenicity.

Fertility of male or female rats was unaffected by clonidine doses as high as 150 mcg/kg (approximately 3 times MRDHD). In a separate experiment, fertility of female rats appeared to be affected at dose levels of 500 to 2000 mcg/kg (10 to 40 times the oral MRDHD on a mg/kg basis; 2 to 8 times the MRDHD on a mg/m^2 basis).

Teratogenic Effects: Pregnancy Category C.

Reproduction studies performed in rabbits at doses up to approximately 3 times the oral maximum recommended daily human dose (MRDHD) of clonidine hydrochloride tablets USP produced no evidence of a teratogenic or embryotoxic potential in rabbits. In rats, however, doses as low as 1/3 the oral MRDHD (1/15 the MRDHD on a mg/m^2 basis) of clonidine were associated with increased resorptions in a study in which dams were treated continuously from 2 months prior to mating. Increased resorptions were not associated with treatment at the same time or at higher dose levels (up to 3 times the oral MRDHD) when the dams were treated on gestation days 6 to 15. Increases in resorption were observed at much higher dose levels (40 times the oral MRDHD on a mg/kg basis;
4 to 8 times the MRDHD on a mg/m^2 basis) in mice and rats treated on gestation days 1 to 14 (lowest dose employed in the study was 500 mcg/kg).

No adequate, well-controlled studies have been conducted in pregnant women. Clonidine crosses the placental barrier (see CLINICAL PHARMACOLOGY, Pharmacokinetics). Because animal reproduction studies are not always predictive of human response, this drug should be used during pregnancy only if clearly needed.

Nursing Mothers

As clonidine hydrochloride is excreted in human milk, caution should be exercised when clonidine hydrochloride tablets USP are administered to a nursing woman.

Pediatric Use

Safety and effectiveness in pediatric patients have not been established in adequate and well-controlled trials (see WARNINGS, Withdrawal).

ADVERSE REACTIONS

Most adverse effects are mild and tend to diminish with continued therapy. The most frequent (which appear to be dose-related) are dry mouth, occurring in about 40 of 100 patients; drowsiness, about 33 in 100; dizziness, about 16 in 100; constipation and sedation, each about 10 in 100.

The following less frequent adverse experiences have also been reported in patients receiving clonidine hydrochloride tablets USP, but in many cases patients were receiving concomitant medication and a causal relationship has not been established.

Body as a Whole: Fatigue, fever, headache, pallor, weakness, and withdrawal syndrome. Also reported were a weakly positive Coombs’ test and increased sensitivity to alcohol.

Cardiovascular: Bradycardia, congestive heart failure, electrocardiographic abnormalities (i.e., sinus node arrest, junctional bradycardia, high degree AV block and arrhythmias), orthostatic symptoms, palpitations, Raynaud’s phenomenon, syncope, and tachycardia. Cases of sinus bradycardia and atrioventricular block have been reported, both with and without the use of concomitant digitalis.

Central Nervous System: Agitation, anxiety, delirium, delusional perception, hallucinations (including visual and auditory), insomnia, mental depression, nervousness, other behavioral changes, paresthesia, restlessness, sleep disorder, and vivid dreams or nightmares.

Dermatological: Alopecia, angioneurotic edema, hives, pruritus, rash, and urticaria.

Gastrointestinal: Abdominal pain, anorexia, constipation, hepatitis, malaise, mild transient abnormalities in liver function tests, nausea, parotitis, pseudo-obstruction (including colonic pseudo-obstruction), salivary gland pain, and vomiting.

Genitourinary: Decreased sexual activity, difficulty in micturition, erectile dysfunction, loss of libido, nocturia, and urinary retention.

Hematologic: Thrombocytopenia.

Metabolic: Gynecomastia, transient elevation of blood glucose or serum creatine phosphokinase, and weight gain.

Musculoskeletal: Leg cramps and muscle or joint pain.

Oro-otolaryngeal: Dryness of the nasal mucosa.

Ophthalmological: Accommodation disorder, blurred vision, burning of the eyes, decreased lacrimation, and dryness of eyes.

OVERDOSAGE

Hypertension may develop early and may be followed by hypotension, bradycardia, respiratory depression, hypothermia, drowsiness, decreased or absent reflexes, weakness, irritability and miosis. The frequency of CNS depression may be higher in children than adults. Large overdoses may result in reversible cardiac conduction defects or dysrhythmias, apnea, coma and seizures. Signs and symptoms of overdose generally occur within 30 minutes to two hours after exposure. As little as 0.1 mg of clonidine has produced signs of toxicity in children.

There is no specific antidote for clonidine overdosage. Clonidine overdosage may result in the rapid development of CNS depression; therefore, induction of vomiting with ipecac syrup is not recommended. Gastric lavage may be indicated following recent and/or large ingestions. Administration of activated charcoal and/or a cathartic may be beneficial. Supportive care may include atropine sulfate for bradycardia, intravenous fluids and/or vasopressor agents for hypotension and vasodilators for hypertension. Naloxone may be a useful adjunct for the management of clonidine-induced respiratory depression, hypotension and/or coma; blood pressure should be monitored since the administration of naloxone has occasionally resulted in paradoxical hypertension. Tolazoline administration has yielded inconsistent results and is not recommended as first-line therapy. Dialysis is not likely to significantly enhance the elimination of clonidine.

The largest overdose reported to date involved a 28-year old male who ingested 100 mg of clonidine hydrochloride powder. This patient developed hypertension followed by hypotension, bradycardia, apnea, hallucinations, semicoma, and premature ventricular contractions. The patient fully recovered after intensive treatment. Plasma clonidine levels were 60 ng/ml after 1 hour, 190 ng/ml after 1.5 hours, 370 ng/ml after 2 hours, and 120 ng/ml after 5.5 and 6.5 hours. In mice and rats, the oral LD50 of clonidine is 206 and 465 mg/kg, respectively.

DOSAGE AND ADMINISTRATION

Adults

The dose of clonidine hydrochloride tablets USP must be adjusted according to the patient’s individual blood pressure response. The following is a general guide to its administration.

Initial Dose

0.1 mg tablet twice daily (morning and bedtime). Elderly patients may benefit from a lower initial dose.

Maintenance Dose

Further increments of 0.1 mg per day may be made at weekly intervals if necessary until the desired response is achieved. Taking the larger portion of the oral daily dose at bedtime may minimize transient adjustment effects of dry mouth and drowsiness. The therapeutic doses most commonly employed have ranged from 0.2 mg to 0.6 mg per day given in divided doses. Studies have indicated that 2.4 mg is the maximum effective daily dose, but doses as high as this have rarely been employed.

Renal Impairment

Patients with renal impairment may benefit from a lower initial dose. Patients should be carefully monitored. Since only a minimal amount of clonidine is removed during routine hemodialysis, there is no need to give supplemental clonidine following dialysis.

HOW SUPPLIED

Clonidine hydrochloride tablets USP are supplied as follows:

Clonidine hydrochloride tablets USP 0.1 mg, yellow, round, debossed MP 657 on one side and plain on the other side.

NDC 68071-4545-1 BOTTLES OF 12

NDC 68071-4545-3 BOTTLES OF 30

NDC 68071-4545-2 BOTTLES OF 120

NDC 68071-4545-8 BOTTLES OF 180

Store at 20° to 25°C (68° to 77°F).

[See USP Controlled Room Temperature]

DISPENSE IN TIGHT, LIGHT-RESISTANT CONTAINER.

Address medical inquiries to: 1-877-541-5504.

Manufactured by: Frontida BioPharm, Inc

Philadelphia, PA 19124

Distributed by: TruPharma, LLC

Tampa, FL 33609

Rev00, March 2017